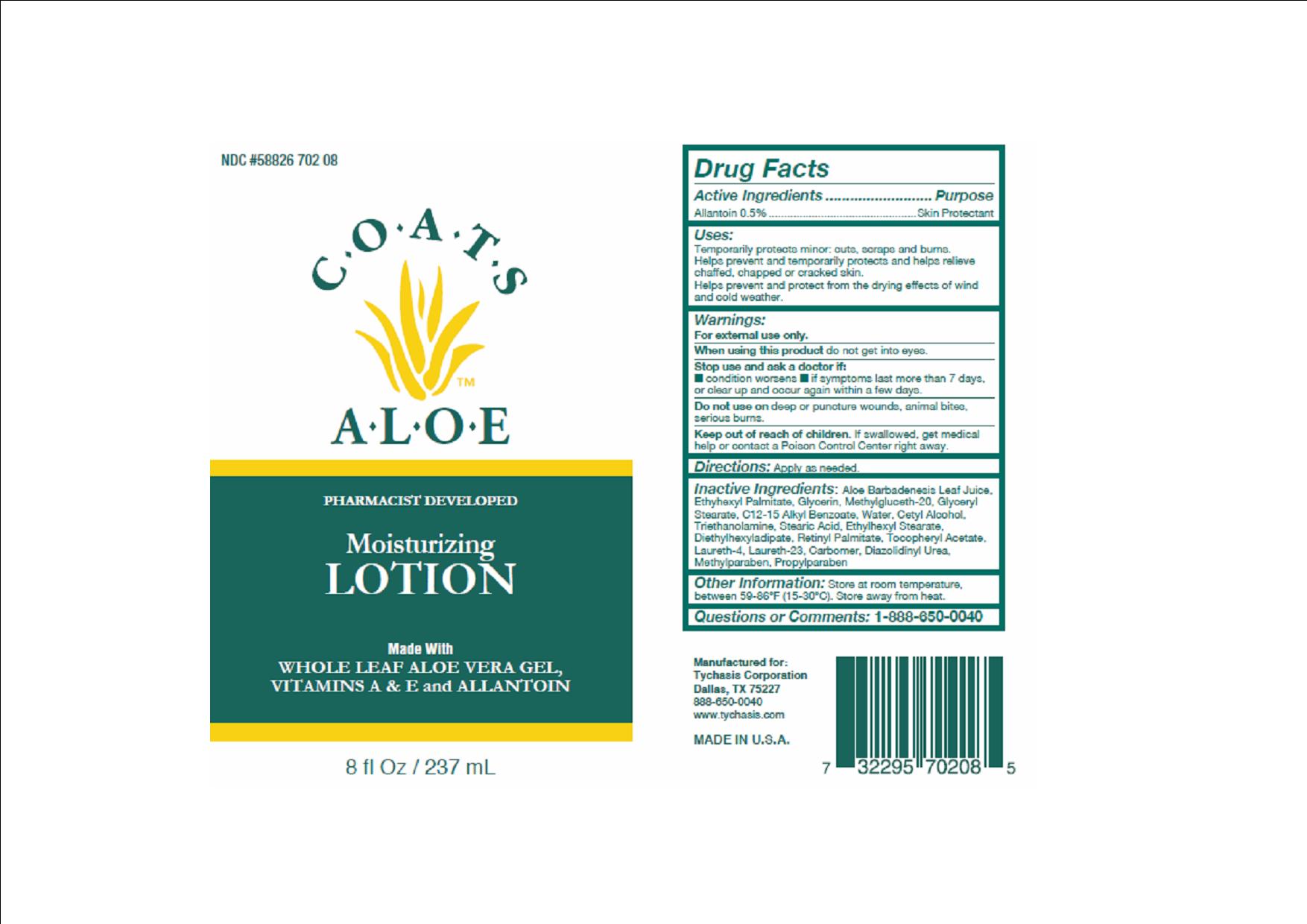 DRUG LABEL: COATS ALOE
NDC: 58826-702 | Form: LOTION
Manufacturer: TYCHASIS CORPORATION
Category: otc | Type: HUMAN OTC DRUG LABEL
Date: 20151109

ACTIVE INGREDIENTS: ALLANTOIN 0.5 g/100 mL
INACTIVE INGREDIENTS: ETHYLHEXYL PALMITATE; ALOE VERA LEAF; BOROGLYCERIN; METHYL GLUCETH-20; ETHYLHEXYL STEARATE; GLYCERYL STEARATE SE; C12-15 ALKYL BENZOATE; CETYL ALCOHOL; STEARIC ACID; DIETHYLHEXYL ADIPATE; VITAMIN A PALMITATE; TOCOPHEROL; LAURETH-4; LAURETH-23; DIAZOLIDINYL UREA; METHYLPARABEN; WATER; PROPYLPARABEN

COATS ALOE LOTION 85%

Active Ingredient

Allantoin 0.5%

Purpose

Skin protectant

Warnings

For external use only.

When using this product do not get into eyes.

Stop use and ask a doctor if:

- condition worsens
- symptoms last more than 7 days or clear up and occur again within a few days

Do not use on deep puncture wounds, animals bites, serious burns.

Uses

Temporarily protects minor

- cuts
- scrapes
- burns

Helps prevent and temporarily protects and helps relieve chaffed, chapped or cracked skin.

Helps prevent and protect from the drying effects of wind and cold weather.

Keep out of reach of children

If swallowed, get medical help or contact a Poison Control Center right away.

Directions

Apply as needed.

Inactive Ingredients

aloe barbadenesis leaf juice, ethylhexyl palmitate, glycerin, methyl gluceth-20, glyceryl stearate, C12-15 alkyl benzoate, water, cetyl alcohol, triethanolamine, stearice acid, ethylhexyl stearate, diethylhexyl adipate, retinyl palmitate, tocopheryl acetate, laureth-4, laureth-23, carbomer, diazolidinyl urea, methylparaben, propylparaben